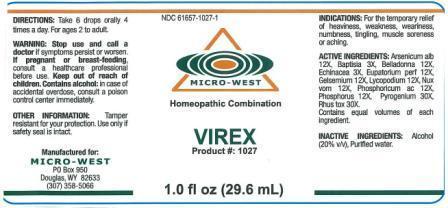 DRUG LABEL: VIREX
NDC: 61657-1027 | Form: LIQUID
Manufacturer: White Manufacturing Inc. DBA Micro West
Category: homeopathic | Type: HUMAN OTC DRUG LABEL
Date: 20140812

ACTIVE INGREDIENTS: ARSENIC TRIOXIDE 12 [hp_X]/30 mL; ECHINACEA, UNSPECIFIED 3 [hp_X]/30 mL; GELSEMIUM SEMPERVIRENS ROOT 12 [hp_X]/30 mL; STRYCHNOS NUX-VOMICA SEED 12 [hp_X]/30 mL; LYCOPODIUM CLAVATUM SPORE 12 [hp_X]/30 mL; ATROPA BELLADONNA 12 [hp_X]/30 mL; RANCID BEEF 30 [hp_X]/30 mL; TOXICODENDRON PUBESCENS LEAF 30 [hp_X]/30 mL; EUPATORIUM PERFOLIATUM FLOWERING TOP 12 [hp_X]/30 mL; BAPTISIA TINCTORIA 3 [hp_X]/30 mL; PHOSPHORUS 12 [hp_X]/30 mL; FOSCOLIC ACID 12 [hp_X]/30 mL
INACTIVE INGREDIENTS: ALCOHOL

Drug Facts

INACTIVE INGREDIENTS

Alcohol (20% v/v). Purified water

Purpose

FOR THE TEMPORARY RELIEF OF HEAVINESS, WEAKNESS, WEARINESS, NUMBNESS, TINGLING, MUSCLE SORENESS OR ACHING

Keep out of reach of children

INDICATIONS

INDICATIONS: FOR THE TEMPORARY RELIEF OF HEAVINESS, WEAKNESS, WEARINESS, NUMBNESS, TINGLING, MUSCLE SORENESS OR ACHING

Warning

WARNING: Stop use and call a doctor if symptoms persist or worsen.Contains alcohol: in case of accidental overdose, consult a poison control center immediately

PREGNANCY OR BREAST FEEDING

If pregnant or breast-feeding, consult a healthcare professional before use

SAFETY

Other information: Tamper resistant for your protection. Use only if safety seal is intact

Directions

DIRECTIONS: Take 6 drops, 4 times a day. For ages 2 to adult

Active ingredient

Arsenicum alb 12X

Baptisia 3X

Belladonna 12X

Echinacea 3X

Eupatorium perf 12X

Gelsenium 12X

Lycopodium 12X

Nux vom 12X

Phosphoricum ac 12X

Phos 12X

Pyrogenium 30X

Rhus tox 30X

Manufacture

MANUFACTURED FOR

MICRO WEST

P.O. Box 950

DOUGLAS, WY 82633

1-307-358-5066